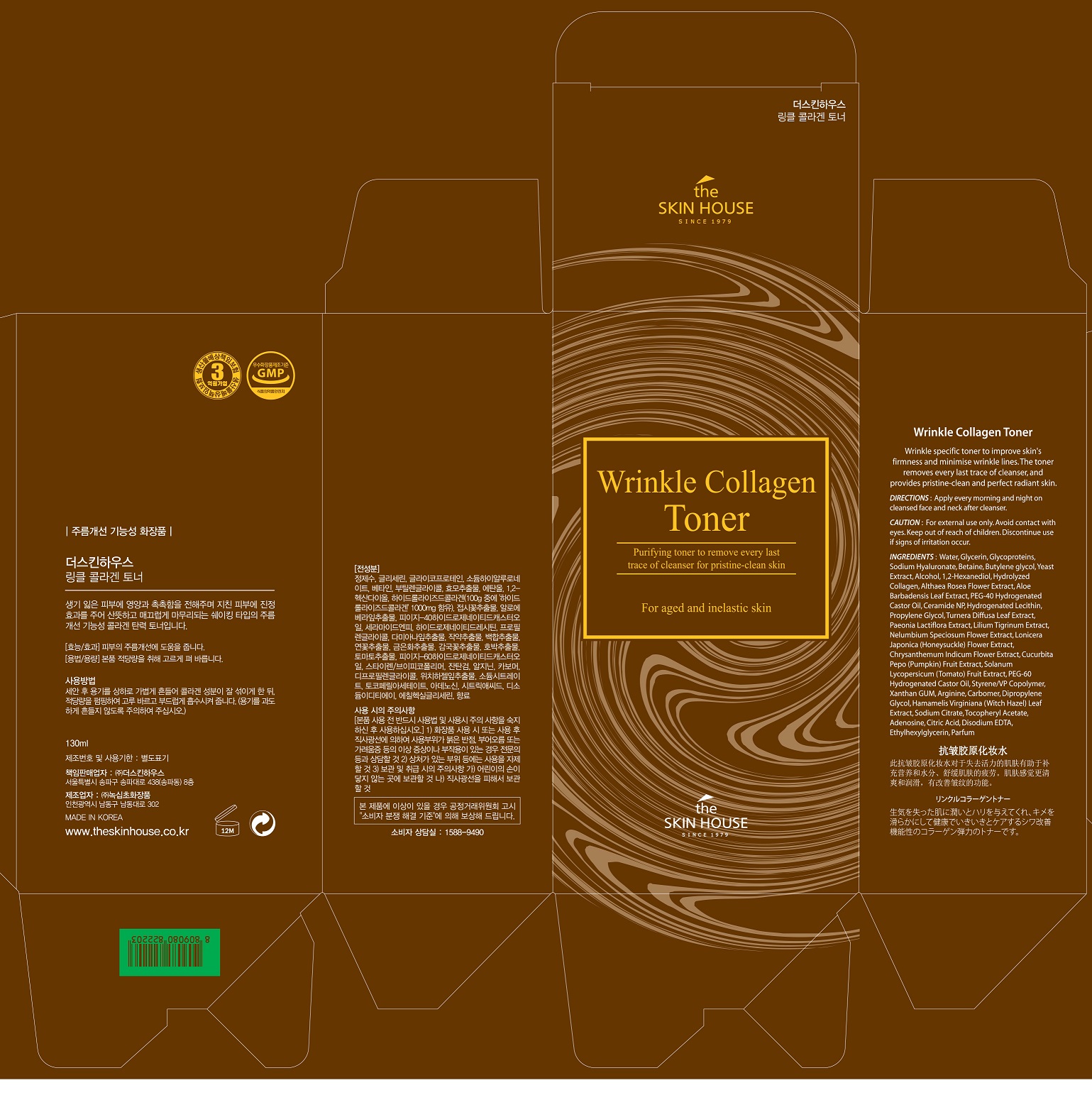 DRUG LABEL: THE SKIN HOUSE Wrinkle Collagen Toner
NDC: 73590-0036 | Form: LIQUID
Manufacturer: NOKSIBCHO cosmetic Co., Ltd.
Category: otc | Type: HUMAN OTC DRUG LABEL
Date: 20200331

ACTIVE INGREDIENTS: ADENOSINE 0.04 g/100 mL
INACTIVE INGREDIENTS: WATER

Drug Facts

ACTIVE INGREDIENT

adenosine

INACTIVE INGREDIENT

Water
Glycerin
Glycoproteins
Betaine
Butylene glycol
Sodium Hyaluronate
Betaine
Alcohol
1,2-Hexanediol
Hydrolyzed Collagen
Althaea Rosea Flower Extract
PEG-40 Hydrogenated Castor Oil
Ceramide NP
Hydrogenated Lecithin
Propylene Glycol
Water
Turnera Diffusa Leaf Extract
Paeonia Lactiflora Extract
Lilium Tigrinum Extract
Nelumbium Speciosum Flower Extract
Lonicera Japonica (Honeysuckle) Flower Extract
Chrysanthemum Indicum Flower Extract
Cucurbita Pepo (Pumpkin) Fruit Extract
Solanum Lycopersicum (Tomato) Fruit Extract
PEG-60 Hydrogenated Castor Oil
Styrene/VP Copolymer
Aloe Barbadensis Leaf Extract
Xanthan GUM
Arginine
Carbomer
Dipropylene Glycol
Hamamelis Virginiana (Witch Hazel) Leaf Extract
Sodium Citrate
Tocopheryl Acetate
Citric Acid
Disodium EDTA
Ethylhexylglycerin
Parfum

PURPOSE

wrinkle care

keep out of reach of the children

INDICATIONS AND USAGE

apply proper amount to the skin

WARNINGS

For external use only
When using this product

■ if the following symptoms occurs after use, stop use and consult with a skin specialist

red specks, swelling, itching

■ don’t use on the part where there is injury, eczema, or dermatitis

Keep out of reach of children

■ if swallowed, get medical help or contact a person control center immediately